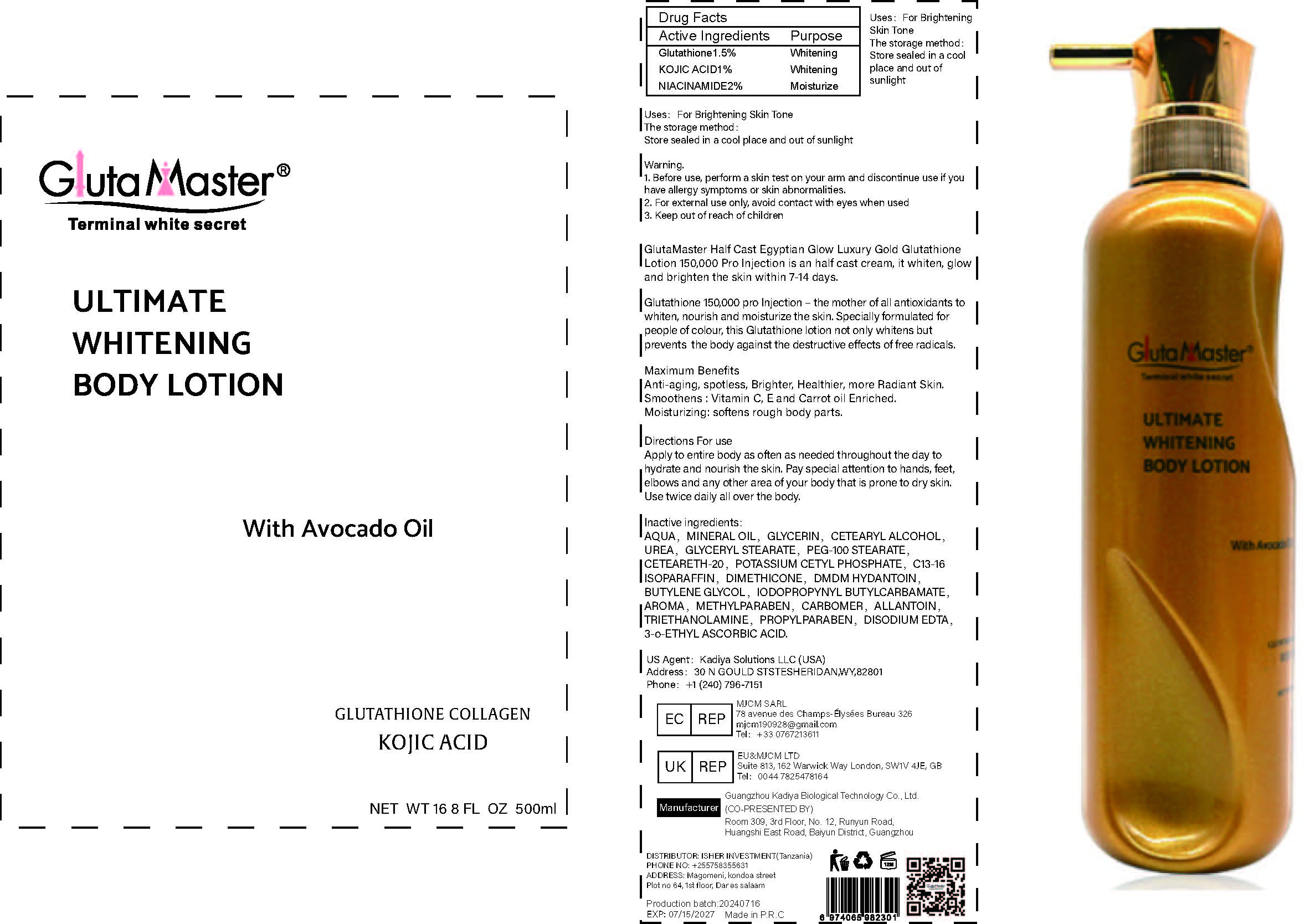 DRUG LABEL: ULTIMATE WHITENING BODYLOTION
NDC: 84423-047 | Form: EMULSION
Manufacturer: Guangzhou Kadiya Biotechnology Co., Ltd.
Category: otc | Type: HUMAN OTC DRUG LABEL
Date: 20241217

ACTIVE INGREDIENTS: NIACINAMIDE 10 g/500 mL; KOJIC ACID 5 g/500 mL; GLUTATHIONE 7.5 g/500 mL
INACTIVE INGREDIENTS: CARBOMER; EDETATE DISODIUM; GLYCERYL STEARATE; CETEARYL ALCOHOL; DMDM HYDANTOIN; BUTYLENE GLYCOL; POTASSIUM CETYL PHOSPHATE; PEG-100 STEARATE; CETEARETH-20; METHYLPARABEN; GLYCERIN; AQUA; MINERAL OIL; ALLANTOIN; PROPYLPARABEN; 3-O-ETHYL ASCORBIC ACID; C13-16 ISOPARAFFIN; DIMETHICONE 1000; IODOPROPYNYL BUTYLCARBAMATE; TRIETHANOLAMINE; UREA

PURPOSE

For Body Skin Whitening and Moisturising

INACTIVE INGREDIENT

AQUA，MINERAL OIL，GLYCERIN，CETEARYL ALCOHOL，UREA，GLYCERYL STEARATE，PEG-100 STEARATE，CETEARETH-20，POTASSIUM CETYL PHOSPHATE，C13-16 ISOPARAFFIN，DIMETHICONE，DMDM HYDANTOIN，BUTYLENE GLYCOL，IODOPROPYNYL BUTYLCARBAMATE，AROMA，METHYLPARABEN，CARBOMER，ALLANTOIN，TRIETHANOLAMINE，PROPYLPARABEN，DISODIUM EDTA，3-o-ETHYL ASCORBIC ACID

WARNINGS

1、For external use only, avoid contact with eyes when used
2、Keep out of reach of children

INDICATIONS AND USAGE

Maximum BenefitsAnti-aging, spotless, Brighter, Healthier, more Radiant Skin Smoothens : Vitamin C, E and Carrot oil Enriched Moisturizing: softens rough body parts.

DOSAGE AND ADMINISTRATION

Directions For useApply to entire body as often as needed throughout the day tohydrate and nourish the skin. Pay special attention to hands, feet,elbows and any other area of your body that is prone to dry skin.Use twice daily all over the body.

KEEP OUT OF REACH OF CHILDREN SECTION

Active Ingredients
Glutathione1.5%
KOJIC ACID1%
NIACINAMIDE2%

PACKAGE LABEL

Active Ingredients
Glutathione1.5%
KOJIC ACID1%
NIACINAMIDE2%

Uses：
For Body Skin Whitening and Moisturising
The storage method：
Store sealed in a cool place and out of sunlight

Warning.
1、For external use only, avoid contact with eyes when used
2、Keep out of reach of children

Inactive ingredients：
AQUA，MINERAL OIL，GLYCERIN，CETEARYL ALCOHOL，UREA，GLYCERYL STEARATE，PEG-100 STEARATE，CETEARETH-20，POTASSIUM CETYL PHOSPHATE，C13-16 ISOPARAFFIN，DIMETHICONE，DMDM HYDANTOIN，BUTYLENE GLYCOL，IODOPROPYNYL BUTYLCARBAMATE，AROMA，METHYLPARABEN，CARBOMER，ALLANTOIN，TRIETHANOLAMINE，PROPYLPARABEN，DISODIUM EDTA，3-o-ETHYL ASCORBIC ACID